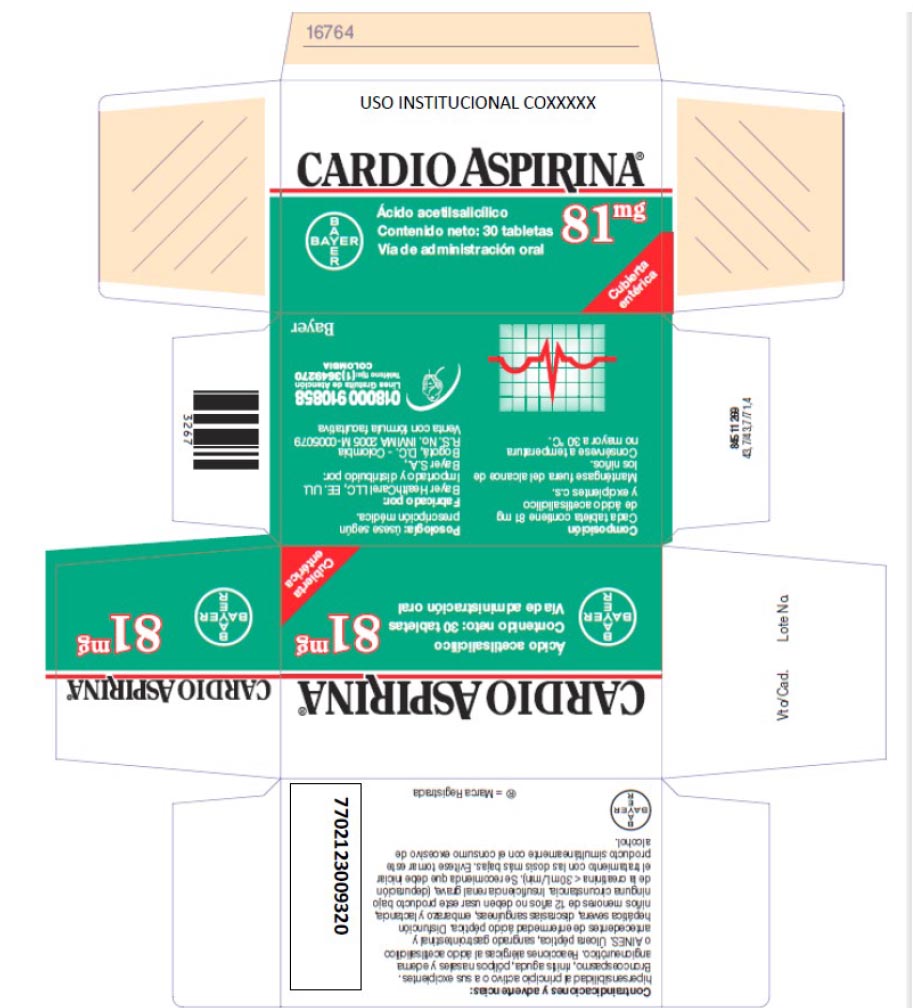 DRUG LABEL: Cardioaspirina Tabletas
NDC: 0280-2095 | Form: TABLET, COATED
Manufacturer: Bayer Healthcare LLC
Category: otc | Type: HUMAN OTC DRUG LABEL
Date: 20260108

ACTIVE INGREDIENTS: 5-BROMO-2-ACETYLSALICYLIC ACID 81 mg/1 1
INACTIVE INGREDIENTS: CELLULOSE, MICROCRYSTALLINE; LACTOSE MONOHYDRATE; STARCH, PREGELATINIZED CORN; POWDERED CELLULOSE; CROSCARMELLOSE SODIUM; METHACRYLIC ACID; POLYSORBATE 80; SODIUM LAURYL SULFATE; TRIACETIN; WATER

Cardioaspirina 81 mg. enteric coated tablet